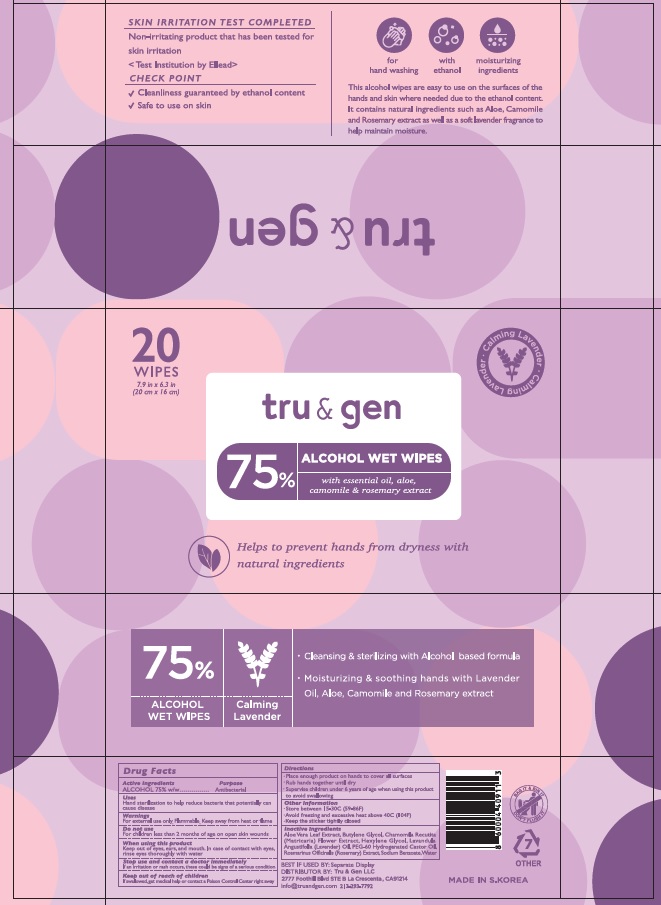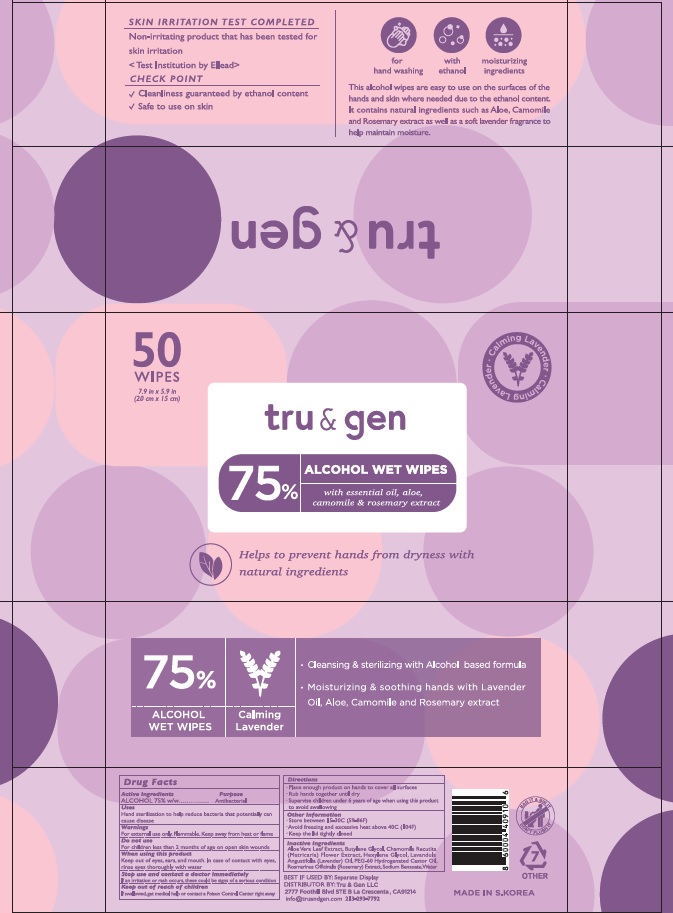 DRUG LABEL: TRU AND GEN 75 PERCENT ALCOHOL WET WIPES
NDC: 74002-5060 | Form: CLOTH
Manufacturer: DongbangCosmetics Co., ltd.
Category: otc | Type: HUMAN OTC DRUG LABEL
Date: 20200831

ACTIVE INGREDIENTS: Alcohol 0.75 1/1 1
INACTIVE INGREDIENTS: ALOE VERA LEAF; Butylene Glycol; CHAMOMILE; Hexylene Glycol; LAVENDER OIL; PEG-60 Hydrogenated Castor Oil; ROSEMARY; Sodium Benzoate; Water

ACTIVE INGREDIENT

Alcohol 75% w/w

INACTIVE INGREDIENTS

Aloe Vera Leaf Extract, Butylene Glycol, Chamomila Recutita (Matricaria) Flower Extract, Hexylene Glycol, Lavandula Angustifolia (Lavender) Oil, PEG-60 Hydrogenated Castor Oil, Rosmarinus Officinalis (Rosemary) Extract, Sodium Benzoate, Water

PURPOSE

Antibacterial

WARNINGS

For external use only. Flammable. Keep away from heat or flame

Do not use
- For children less than 2 months of age on open skin wounds

When using this product
keep out of eyes, ears, and mouth. In case of contact with eyes, rinse eyes thoroughly with water

Stop use and contact a doctor immediately
If an irritation or rash occurs, these could be signs of a serious condition

KEEP OUT OF REACH OF CHILDREN

If swallowed, get medical help or contact a Poison Control Center right away

Uses

Hand sterilization to help reduce bacteria that potentially can cause disease

Directions

- Place enough product on hands to cover all surfaces
- Rub hands together until dry
- Supervise children under 6 years of age when using this product to avoid swallowing

Other Information

- Store between 15-30C (59-86F)
- Avoid freezing and excessive heat above 40C (104F)
- Keep the sticker tightly closed